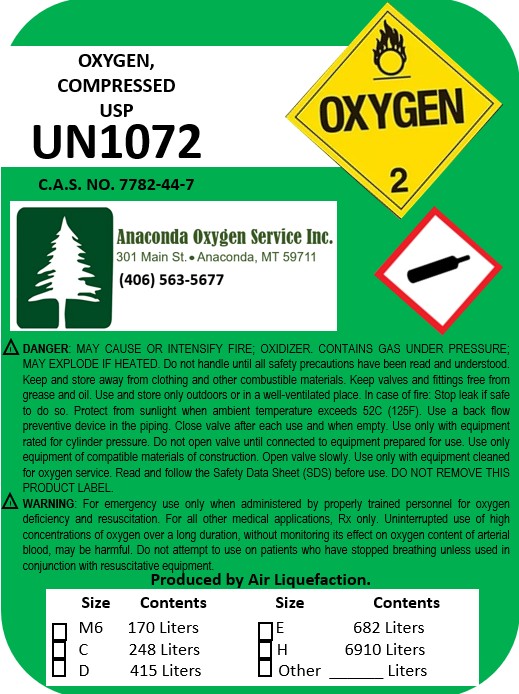 DRUG LABEL: Compressed Oxygen
NDC: 18087-0007 | Form: INHALANT
Manufacturer: James D. Anderson
Category: prescription | Type: HUMAN PRESCRIPTION DRUG LABEL
Date: 20241231

ACTIVE INGREDIENTS: OXYGEN 21 kg/100 L

Drug Certification